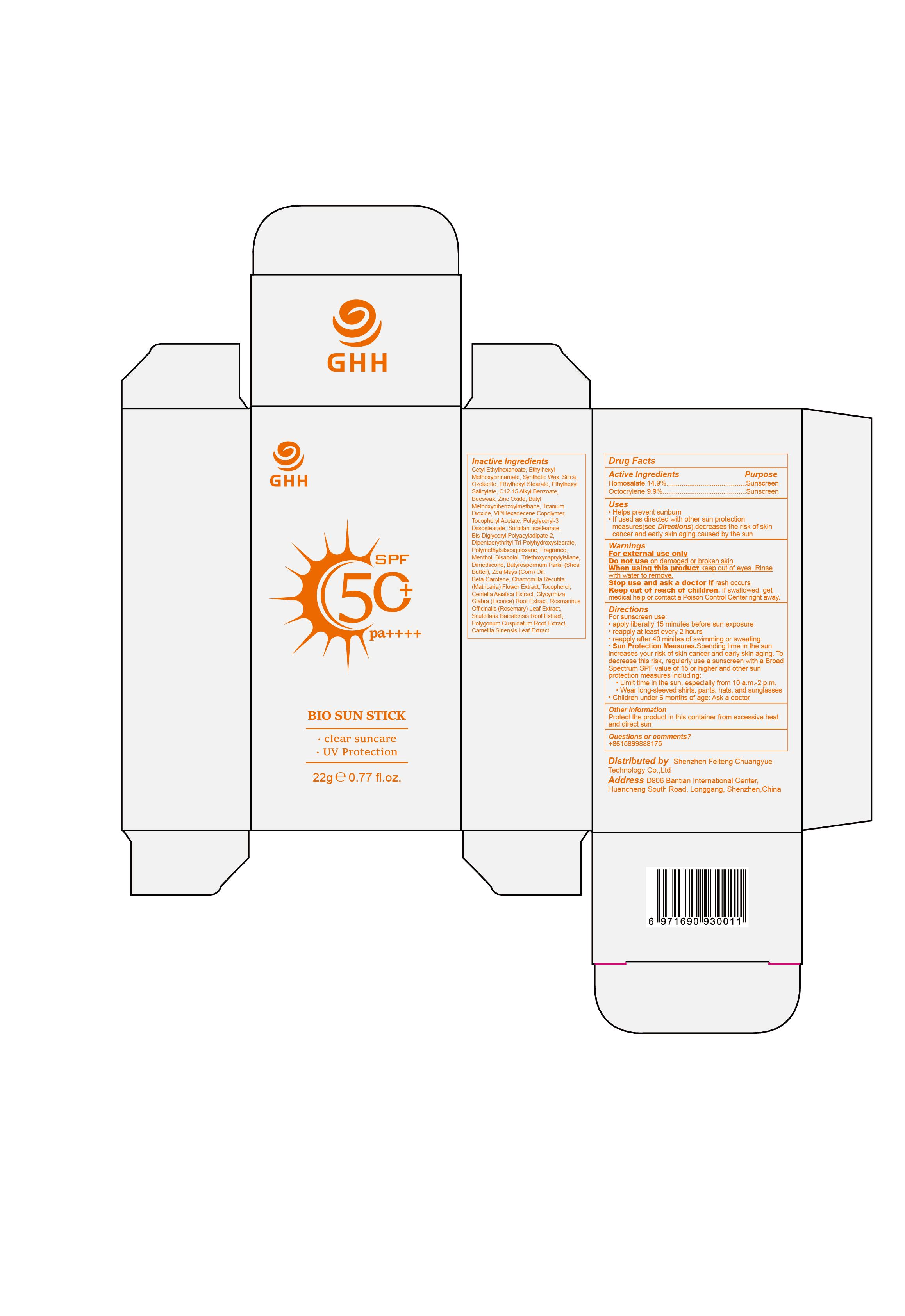 DRUG LABEL: Ghh Bio Sun Stick
NDC: 75779-006 | Form: PASTE
Manufacturer: GUANG DONG 3 INS TECHNOLOGY Co., Ltd
Category: otc | Type: HUMAN OTC DRUG LABEL
Date: 20240617

ACTIVE INGREDIENTS: HOMOSALATE 14.9 g/100 g; OCTOCRYLENE 9.9 g/100 g
INACTIVE INGREDIENTS: ROSEMARY; VINYLPYRROLIDONE/HEXADECENE COPOLYMER; FRAGRANCE 13576; TITANIUM DIOXIDE; ALKYL (C12-15) BENZOATE; GREEN TEA LEAF; OCTISALATE; SORBITAN ISOSTEARATE; ETHYLHEXYL STEARATE; CETYL ETHYLHEXANOATE; DIPENTAERYTHRITYL TRI-POLYHYDROXYSTEARATE; TRIETHOXYCAPRYLYLSILANE; TOCOPHEROL; CENTELLA ASIATICA TRITERPENOIDS; BETA CAROTENE; POLYGONUM CUSPIDATUM ROOT; CHAMOMILE; SILICON DIOXIDE; LEVOMENOL; DIMETHICONE; SCUTELLARIA BAICALENSIS ROOT; ZINC OXIDE; CORN OIL; CERESIN; AVOBENZONE; .ALPHA.-TOCOPHEROL ACETATE; POLYGLYCERYL-3 DIISOSTEARATE; SYNTHETIC WAX (1200 MW); YELLOW WAX; POLYMETHYLSILSESQUIOXANE (4.5 MICRONS); MENTHOL; GLYCYRRHIZA GLABRA; OCTINOXATE; BIS-DIGLYCERYL POLYACYLADIPATE-2; SHEA BUTTER

75779-006

Active Ingredient

Homosalate 14.9%
Octocrylene 9.9%

Purpose

Sunscreen

Use

Helps prevent sunburn
If used as directed with other sun protection measures(see Directions),decreases the risk of skin cancer and early skin aging caused by the sun

Warnings

For external use only

Do not use on damaged or broken skin

When Using

When using this product keep out of eyes. Rinse with water to remove.

Stop Use

Stop use and ask a doctor if rash occurs

Ask Doctor

Children under 6 months of age: Ask a doctor

Keep Oot Of Reach Of Children

Keep out of reach of children.If swallowed,get medical help or contact a Poison Control Center right away.

Directions

For sunscreen use:
apply liberally 15 minutes before sun exposure
reapply at least every 2 hours
reapply after 40 minites of swimming or sweating
Sun Protection Measures.Spending time in the sun increases your risk of skin cancer and early skin aging. To decrease this risk, regularly use a sunscreen with a Broad Spectrum SPF value of 15 or higher and other sun protection measures including:
Limit time in the sun, especially from 10 a.m.-2 p.m.
Wear long-sleeved shirts, pants, hats, and sunglasses
Children under 6 months of age: Ask a doctor

Other information

Protect the product in this container from excessive heat and direct sun

Inactive ingredients

Cetyl Ethylhexanoate,Ethylhexyl Methoxycinnamate,Synthetic Wax,Silica,Ozokerite,Ethylhexyl Stearate,Ethylhexyl Salicylate,C12-15 Alkyl Benzoate,Beeswax,Zinc Oxide,Butyl Methoxydibenzoylmethane,Titanium Dioxide,VP/Hexadecene Copolymer,Tocopheryl Acetate,Polyglyceryl-3 Diisostearate,Sorbitan Isostearate,Bis-Diglyceryl Polyacyladipate-2,Dipentaerythrityl Tri-Polyhydroxystearate,Polymethylsilsesquioxane,Fragrance,Menthol,Bisabolol,Triethoxycaprylylsilane,Dimethicone,Butyrospermum Parkii (Shea Butter),Zea Mays (Corn) Oil,Beta-Carotene,Chamomilla Recutita (Matricaria) Flower Extract,Tocopherol,Centella Asiatica Extract,Glycyrrhiza Glabra (Licorice) Root Extract,Rosmarinus Officinalis (Rosemary) Leaf Extract,Scutellaria Baicalensis Root Extract,Polygonum Cuspidatum Root Extract,Camellia Sinensis Leaf Extract

Questions

+8615899888175